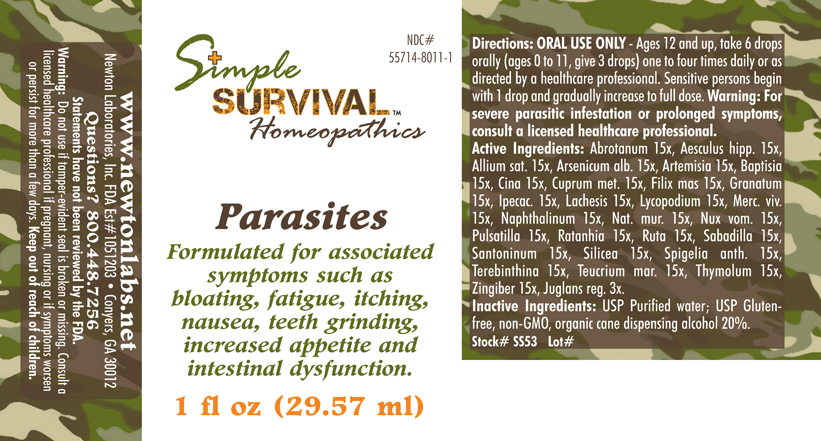 DRUG LABEL: Parasites 
NDC: 55714-8011 | Form: LIQUID
Manufacturer: Newton Laboratories, Inc.
Category: homeopathic | Type: HUMAN OTC DRUG LABEL
Date: 20140415

ACTIVE INGREDIENTS: Artemisia Abrotanum Flowering Top 15 [hp_X]/1 mL; Horse Chestnut 15 [hp_X]/1 mL; Garlic 15 [hp_X]/1 mL; Arsenic Trioxide 15 [hp_X]/1 mL; Artemisia Vulgaris Root 15 [hp_X]/1 mL; Baptisia Tinctoria 15 [hp_X]/1 mL; Artemisia Cina Pre-flowering Top 15 [hp_X]/1 mL; Copper 15 [hp_X]/1 mL; Dryopteris Filix-mas Root 15 [hp_X]/1 mL; Punica Granatum Root Bark 15 [hp_X]/1 mL; Ipecac 15 [hp_X]/1 mL; Lachesis Muta Venom 15 [hp_X]/1 mL; Lycopodium Clavatum Spore 15 [hp_X]/1 mL; Mercury 15 [hp_X]/1 mL; Naphthalene 15 [hp_X]/1 mL; Sodium Chloride 15 [hp_X]/1 mL; Strychnos Nux-vomica Seed 15 [hp_X]/1 mL; Pulsatilla Vulgaris 15 [hp_X]/1 mL; Krameria Lappacea Root 15 [hp_X]/1 mL; Ruta Graveolens Flowering Top 15 [hp_X]/1 mL; Schoenocaulon Officinale Seed 15 [hp_X]/1 mL; Santonin 15 [hp_X]/1 mL; Silicon Dioxide 15 [hp_X]/1 mL; Spigelia Anthelmia 15 [hp_X]/1 mL; Turpentine Oil 15 [hp_X]/1 mL; Teucrium Marum 15 [hp_X]/1 mL; Thymol 15 [hp_X]/1 mL; Ginger 15 [hp_X]/1 mL; English Walnut 3 [hp_X]/1 mL
INACTIVE INGREDIENTS: Alcohol

Parasites

INDICATIONS & USAGE SECTION

Parasites Formulated for associated symptoms such as bloating, fatigue, itching, nausea, teeth grinding, increased appetite and intestinal dysfunction.

DOSAGE & ADMINISTRATION SECTION

Directions: ORAL USE ONLY - Ages 12 and up, take 6 drops orally (ages 0 to 11, give 3 drops) one to four times daily or as directed by a healthcare professional. Sensitive persons begin with 1 drop and gradually increase to full dose. Warning: For severe parasitic infestation or prolonged symptoms, consult a licensed healthcare professional.

OTC - ACTIVE INGREDIENT SECTION

Abrotanum 15x, Aesculus hipp. 15x, Allium sat. 15x, Arsenicum alb. 15x, Artemisia 15x, Baptisia 15x, Cina 15x, Cuprum met. 15x, Filix mas 15x, Granatum 15x, Ipecac. 15x, Lachesis 15x, Lycopodium 15x, Merc. viv. 15x, Naphthalinum 15x, Nat. mur. 15x, Nux vom. 15x, Pulsatilla 15x, Ratanhia 15x, Ruta 15x, Sabadilla 15x, Santoninum 15x, Silicea 15x, Spigelia anth. 15x, Terebinthina 15x, Teucrium mar. 15x, Thymolum 15x, Zingiber 15x, Juglans reg. 3x.

OTC - PURPOSE SECTION

Formulated for associated symptoms such as bloating, fatigue, itching, nausea, teeth grinding, increased appetite and intestinal dysfunction.

INACTIVE INGREDIENT SECTION

Inactive Ingredients: USP Purified Water; USP Gluten-free, non-GMO, organic cane dispensing alcohol 20%

QUESTIONS SECTION

www.newtonlabs.net Newton Laboratories, Inc. FDA Est # 1051203 - Conyers, GA 30012
Questions? 1.800.448.7256

WARNINGS SECTION

Warning: Do not use if tamper - evident seal is broken or missing. Consult a licensed healthcare professional if pregnant, nursing or if symptoms worsen or persist for more than a few days. Keep out of reach of children

OTC - PREGNANCY OR BREAST FEEDING SECTION

Consult a licensed healthcare professional if pregnant, nursing or if symptoms worsen or persist for more than a few days

OTC - KEEP OUT OF REACH OF CHILDREN SECTION

Keep out of reach of children.